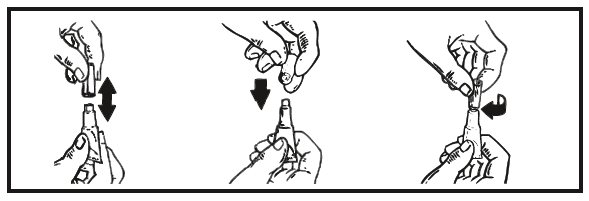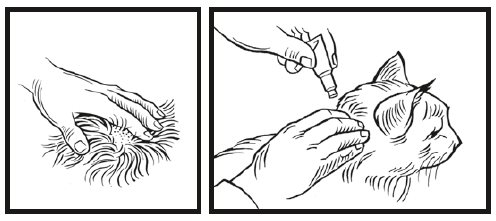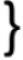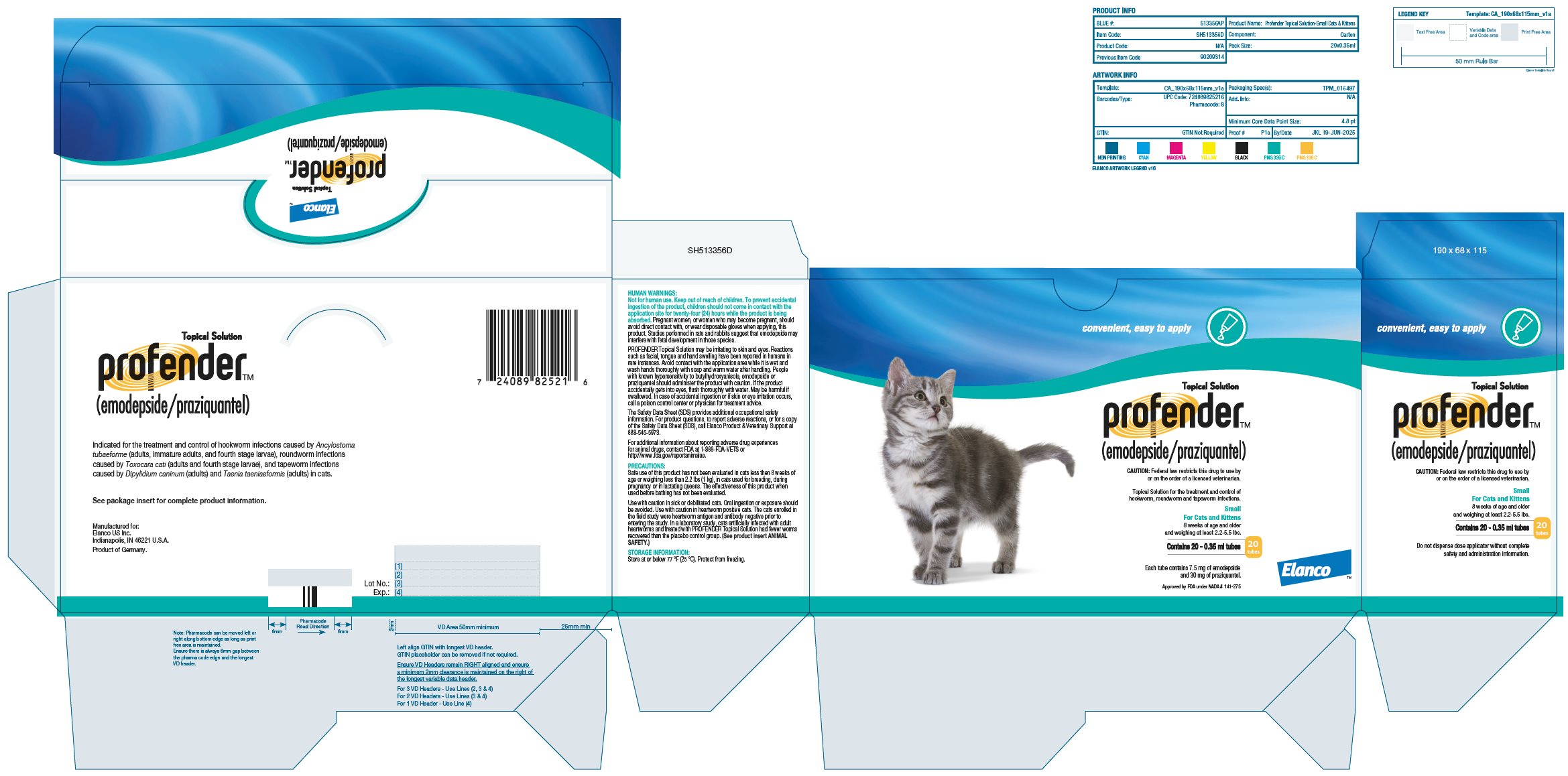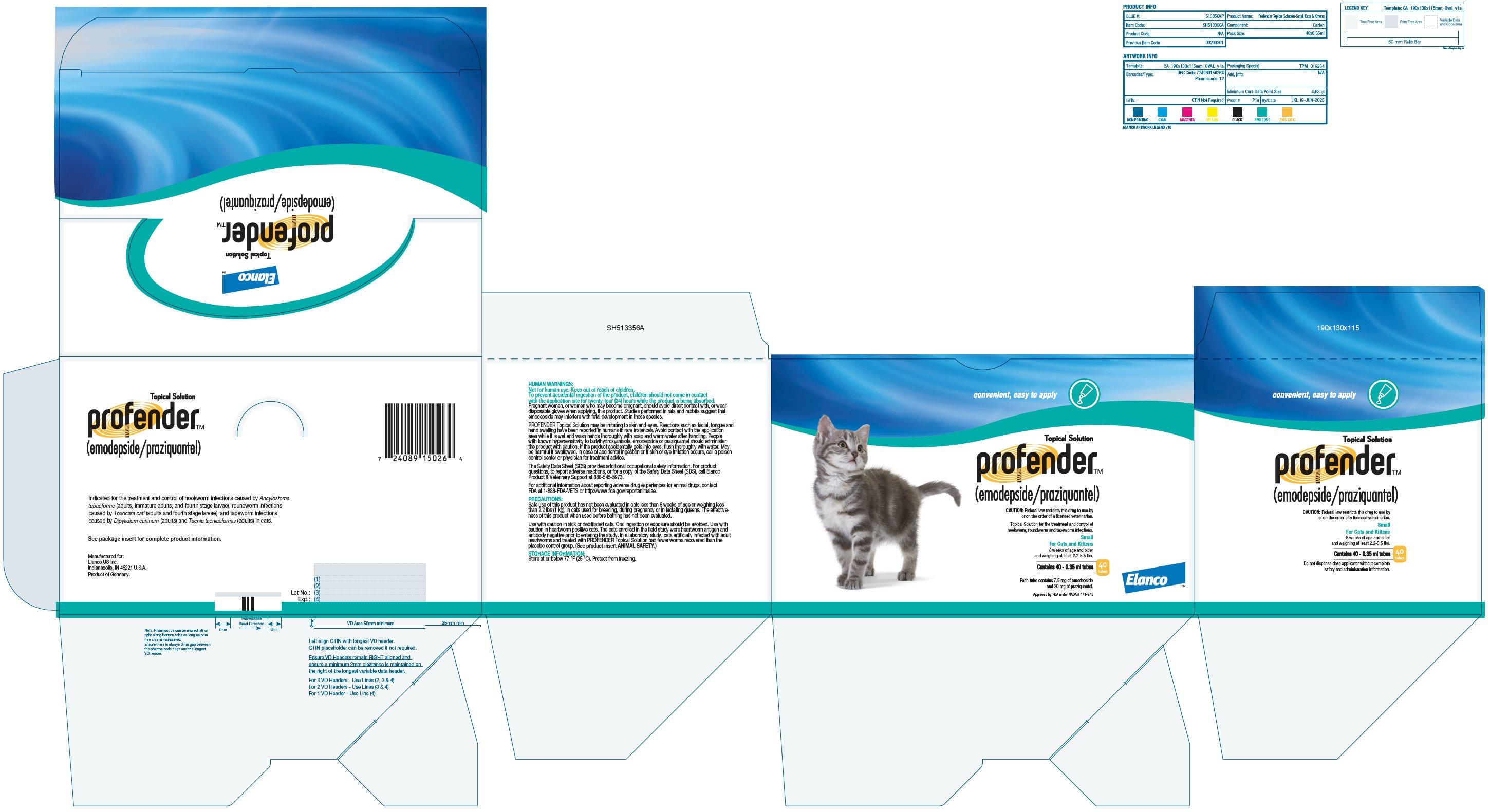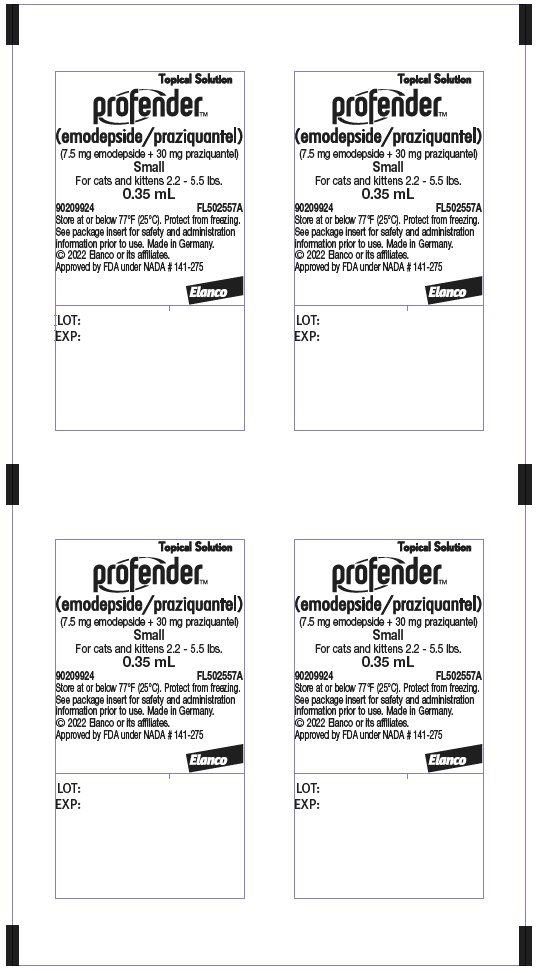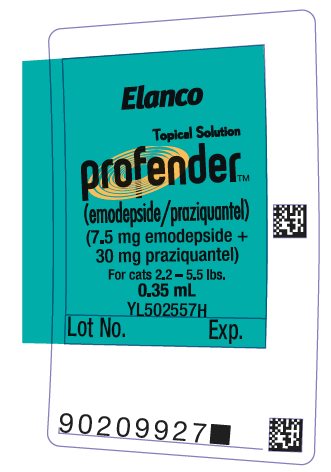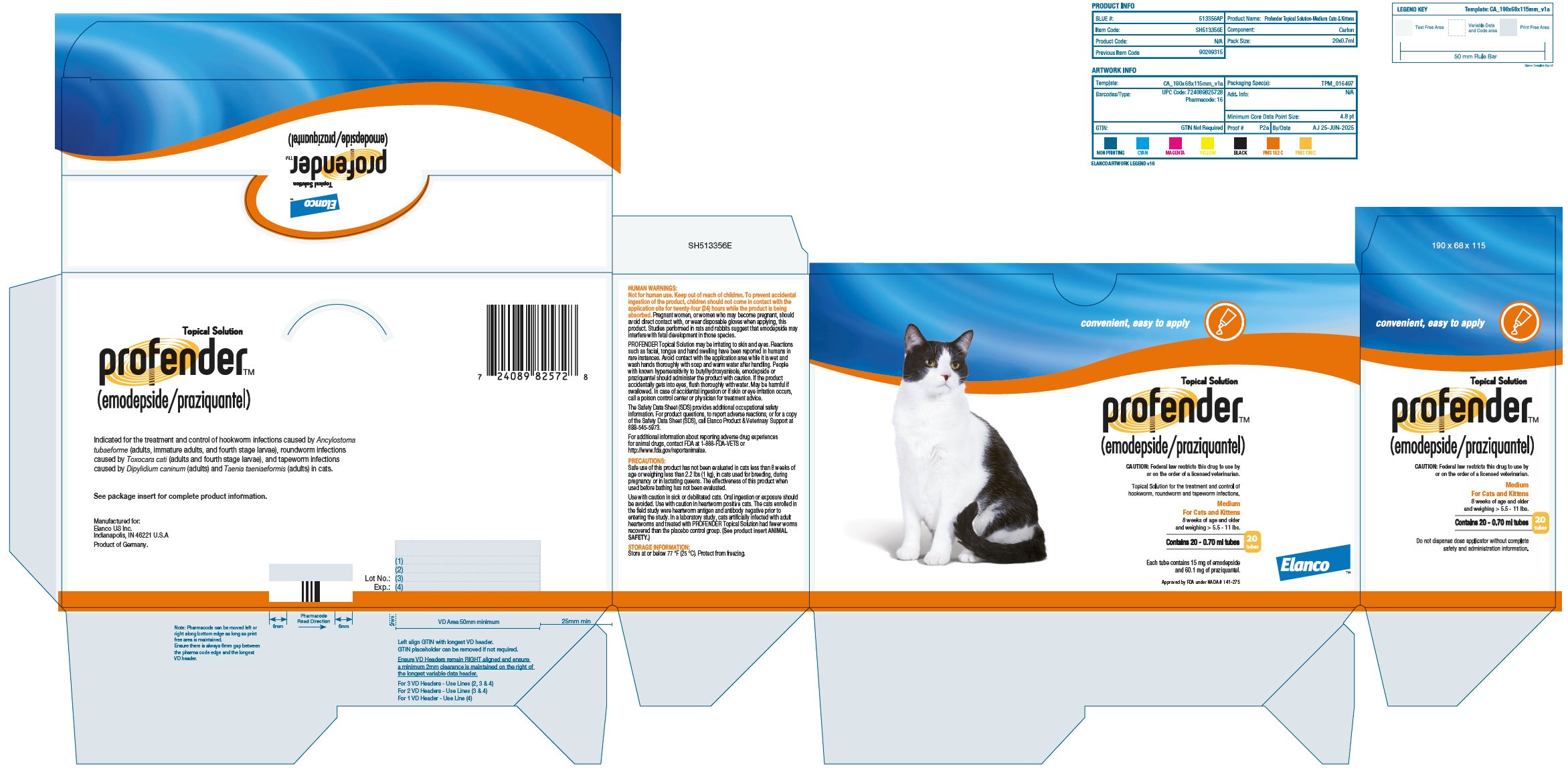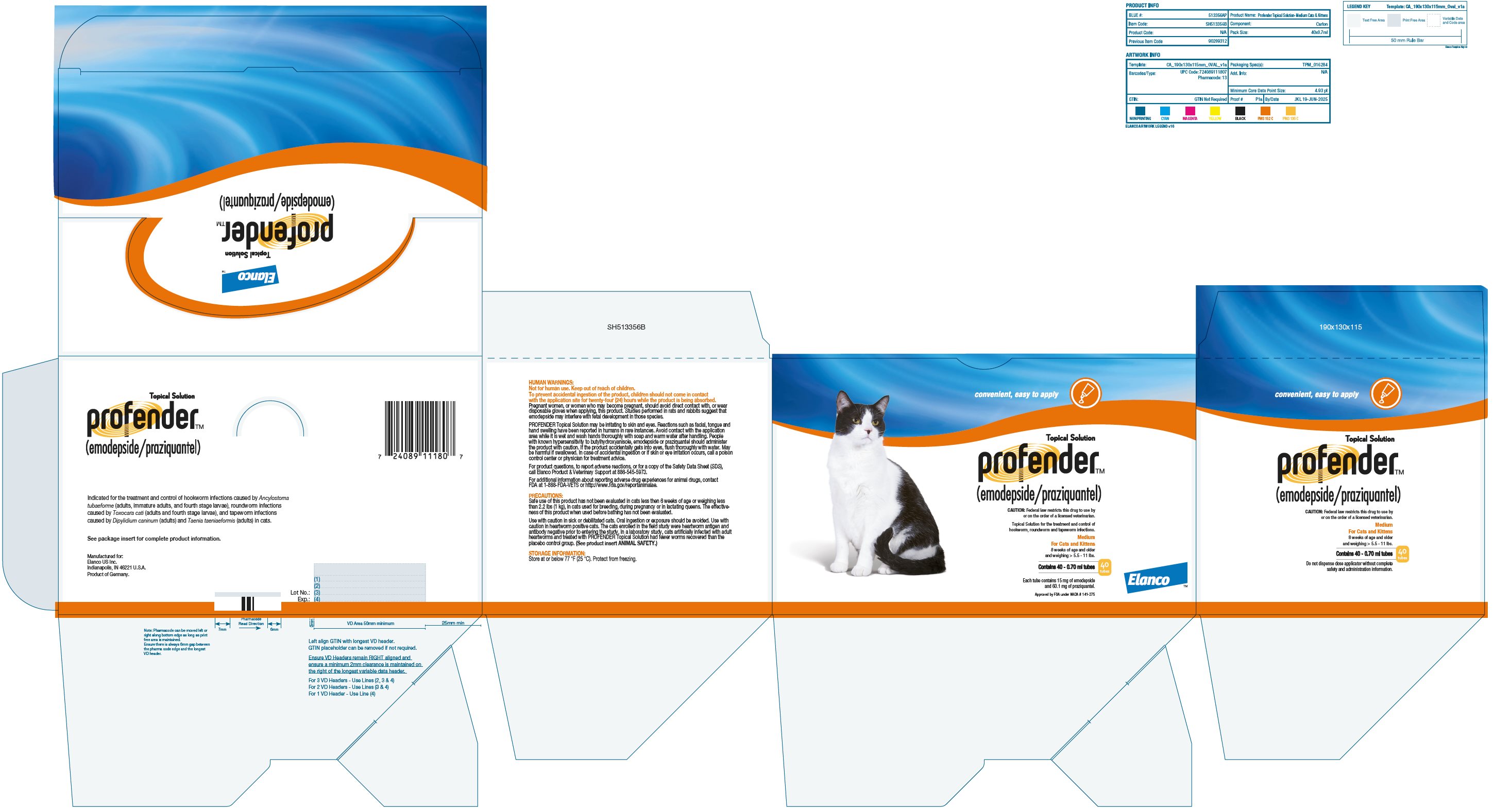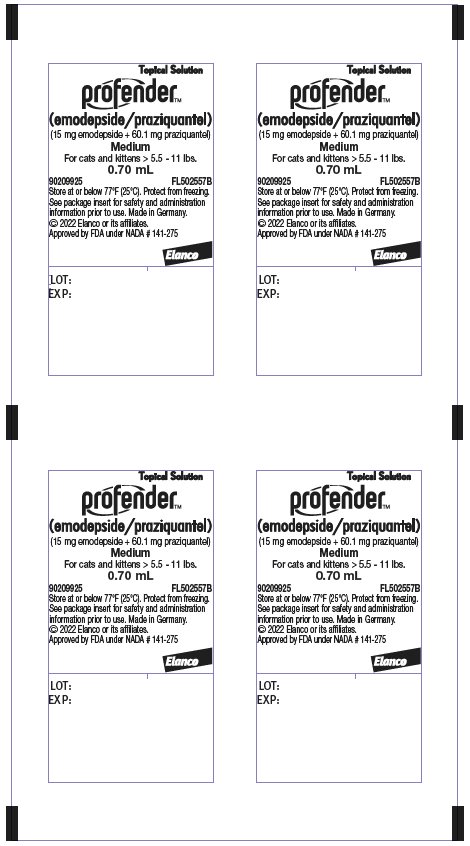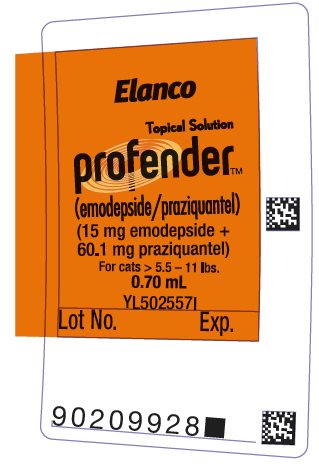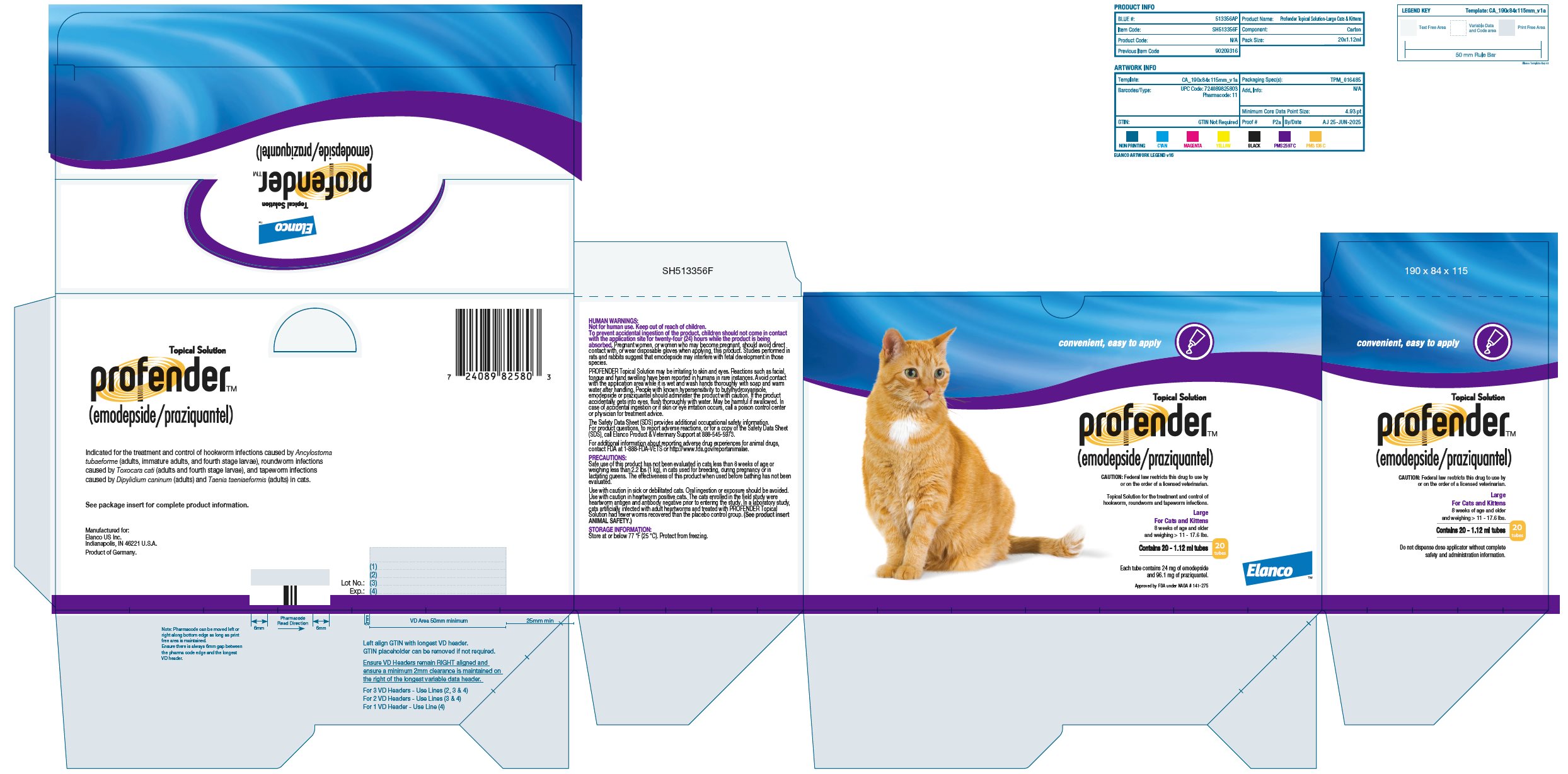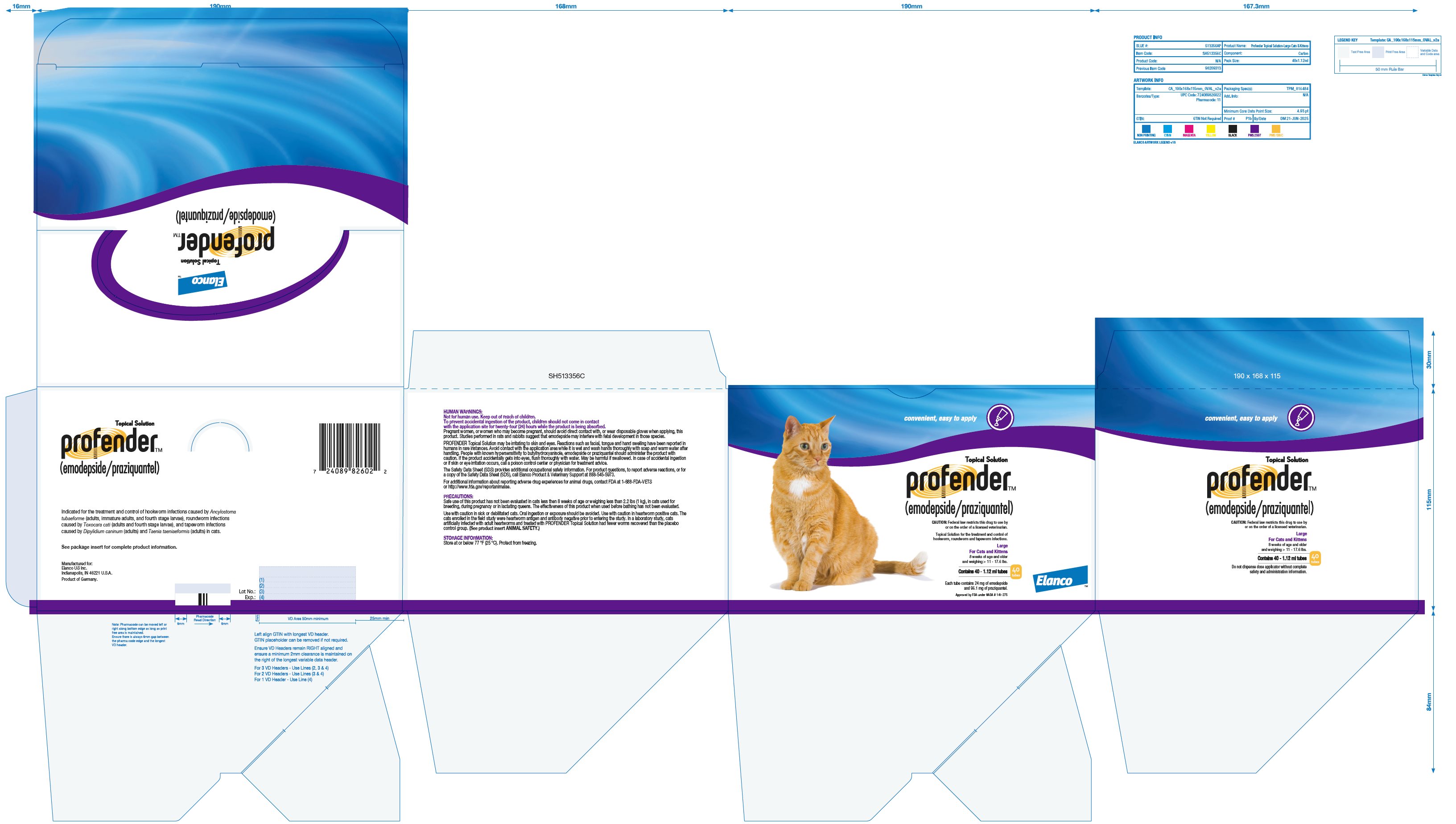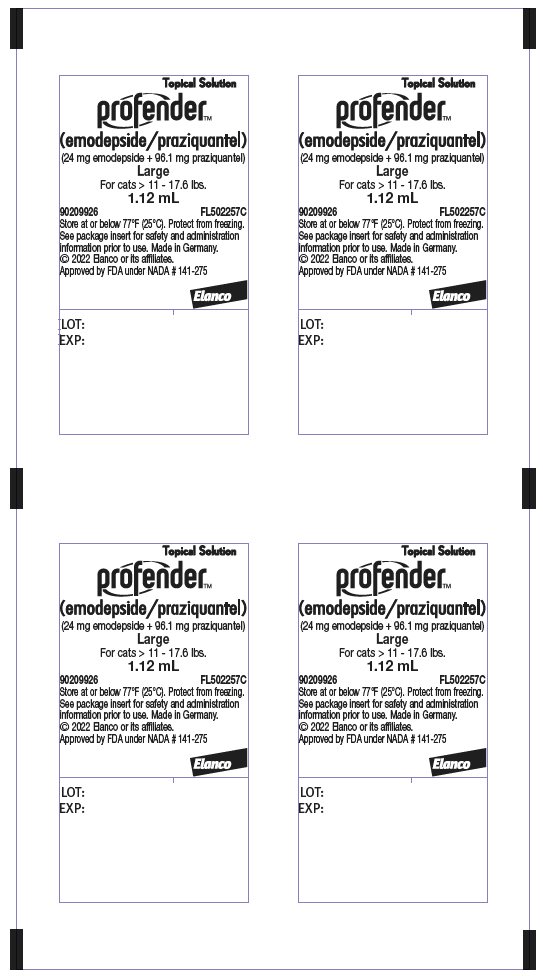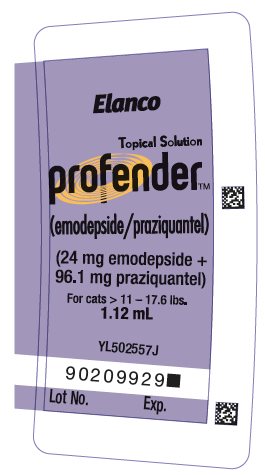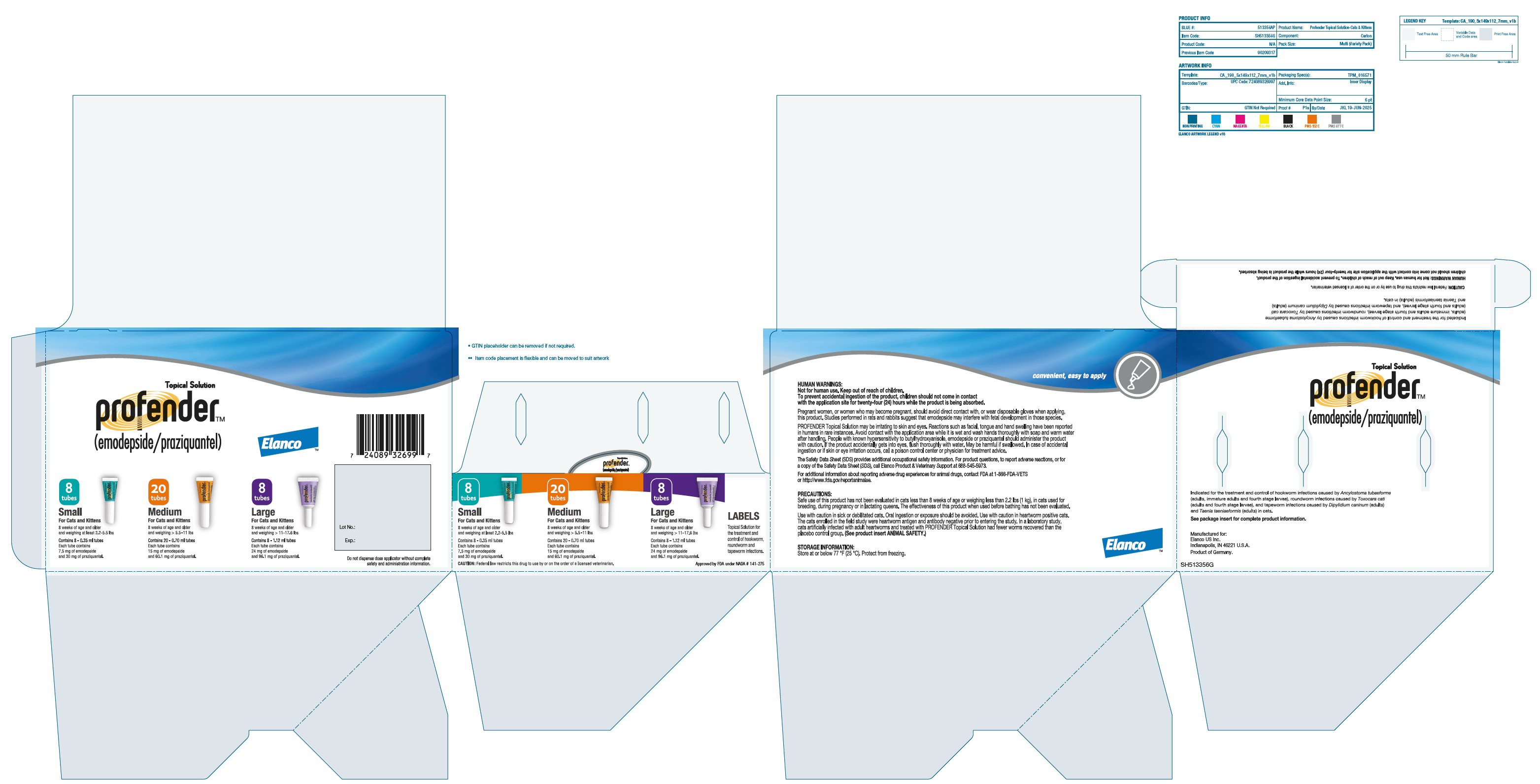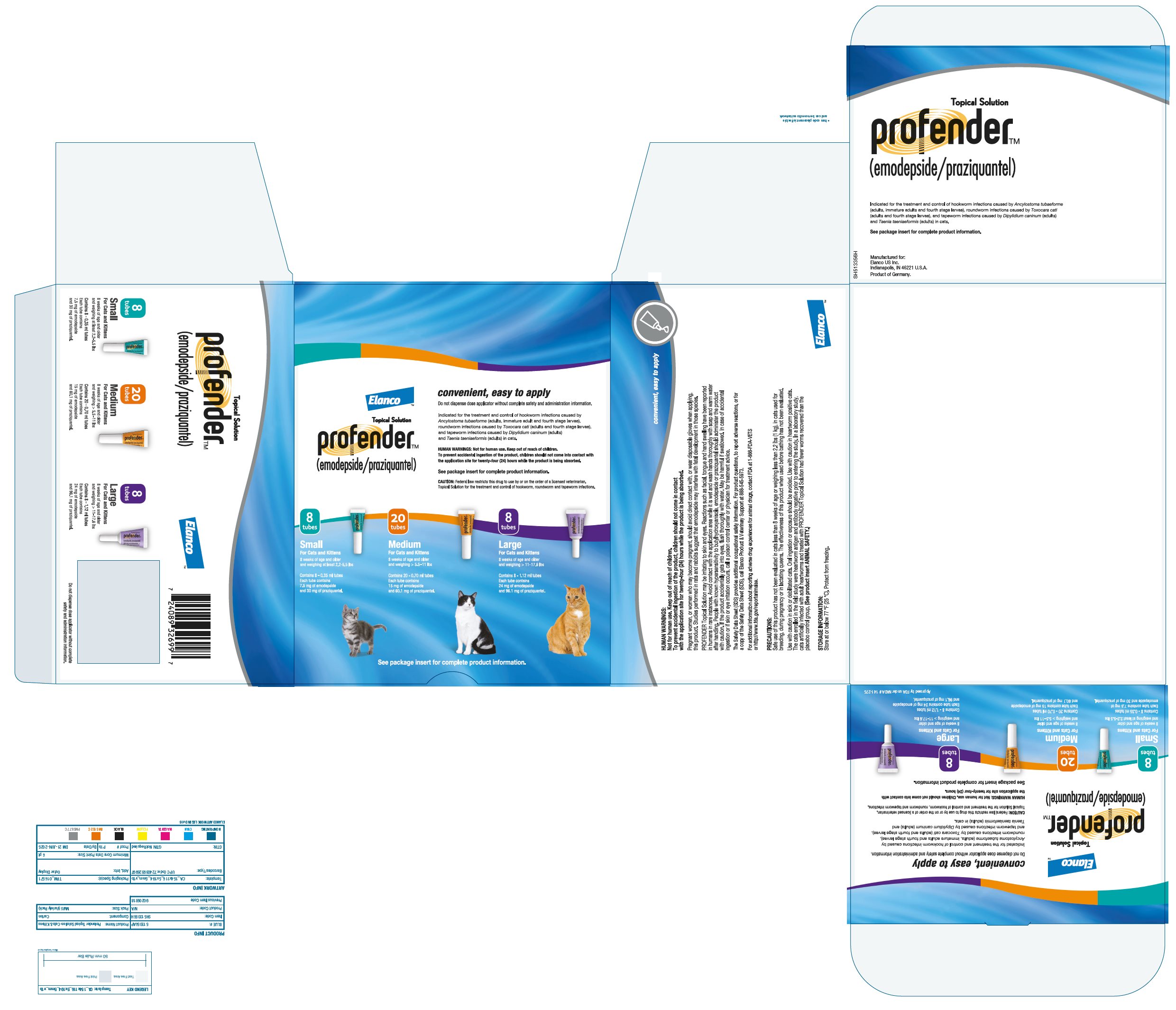 DRUG LABEL: Profender
NDC: 58198-0059 | Form: SOLUTION
Manufacturer: Elanco US Inc.
Category: animal | Type: PRESCRIPTION ANIMAL DRUG LABEL
Date: 20251104

ACTIVE INGREDIENTS: PRAZIQUANTEL 30 mg/0.35 mL; EMODEPSIDE 7.5 mg/0.35 mL

Topical Solution
profender™
(emodepside/praziquantel)

CAUTION: Federal law restricts this drug to use by or on the order of a licensed veterinarian.

Topical Solution for the treatment and control of hookworm, roundworm and tapeworm infections in cats and kittens that are at least 8 weeks of age and weigh at least 2.2 lbs (1 kg).

DESCRIPTION:

PROFENDER [1.98% emodepside/7.94% praziquantel] Topical Solution is a clear yellow ready-to-use solution packaged in single unit dosing applicator tubes for topical (dermal) treatment of cats 8 weeks of age and older and weighing at least 2.2 lbs (1 kg). The formulation and dosage schedule is designed to provide a minimum of 1.36 mg/lb (3 mg/kg) emodepside and 5.45 mg/lb (12 mg/kg) praziquantel based on body weight. Emodepside, a semi-synthetic molecule, is a cyclic depsipeptide. The chemical name is Cyclo [D-2-hydroxypropanoyl-N-methyl-L-leucyl-3-[4-(4-morpholinyl)phenyl]-D-2-hydroxypropanoyl-N-methyl-L-leucyl-D-2-hydroxypropanoyl-N-methyl-L-leucyl-3-[4-(4-morpholinyl)phenyl]-D-2-hydroxypropanoyl-N-methyl-L-leucyl]. Praziquantel is an isoquinoline cestocide. The chemical name is 2-Cyclohexylcarbonyl-1,2,3,6,7,11b-hexahydro-4H-pyrazine-2,1-a-iso-quinoline-4-one.

INDICATIONS:

PROFENDER Topical Solution is indicated for the treatment and control of hookworm infections caused by Ancylostoma tubaeforme (adults, immature adults, and fourth stage larvae), roundworm infections caused by Toxocara cati (adults and fourth stage larvae), and tapeworm infections caused by Dipylidium caninum (adults) and Taenia taeniaeformis (adults) in cats.

DOSAGE AND ADMINISTRATION:

The recommended minimum dose is 1.36 mg/lb (3 mg/kg) emodepside + 5.45 mg/lb (12 mg/kg) praziquantel as a single topical dose. A single treatment is effective and a second treatment should not be necessary. If re-infection occurs, the product can be re-applied after 30 days.

1. Select the package that correctly corresponds with the body weight of the cat. (See Table below.)

Cat Weight* | Profender Topical Solution | Volume (mL) | Emodepside (mg) | Praziquantel (mg)
2.2-5.5 lbs. | Small | 0.35 | 7.5 | 30.0
>5.5-11 lbs. | Medium | 0.70 | 15.0 | 60.1
>11-17.6 lbs. | Large | 1.12 | 24.0 | 96.1
* Cats over 17.6 lbs should be treated with the appropriate combination of tubes.

2. Remove one unit dose tube from the package.
3. While holding the tube in an upright position, remove the cap from the tube.
4. Turn the cap over and place the other end of cap onto the tip of the tube.
5. Twist the cap to break the seal and then remove cap from the tube.

6. Part the hair on the back of the cat’s neck at the base of the head, until the skin is visible.

7. The ensure the entire contents of the tube are administered, place the tip of the tube on the skin and squeeze the entire contents directly onto the skin. Lift tube away from the skin before releasing pressure on the tube.

Do not apply to broken skin or if hair coat is wet. Do not get this product in the cat’s mouth or eyes or allow the cat to lick the application site for one hour. Oral exposure can cause salivation and vomiting. Treatment at the base of the head will minimize the opportunity for ingestion while grooming. In households with multiple pets, keep animals separated to prevent licking of the application site.

Stiff hair, a damp appearance of the hair, or a slight powdery residue may be observed at the treatment site. These effects are temporary and do not affect the safety or effectiveness of the product.

HUMAN WARNINGS:

Not for human use. Keep out of reach of children.

To prevent accidental ingestion of the product, children should not come in contact with the application site for twenty-four (24) hours while the product is being absorbed. Pregnant women, or women who may become pregnant, should avoid direct contact with, or wear disposable gloves when applying, this product. Studies performed in rats and rabbits suggest that emodepside may interfere with fetal development in those species.

PROFENDER Topical Solution may be irritating to skin and eyes. Reactions such as facial, tongue and hand swelling have been reported in humans in rare instances. Avoid contact with the application area while it is wet and wash hands thoroughly with soap and warm water after handling. People with known hypersensitivity to butylhydroxyanisole, emodepside or praziquantel should administer the product with caution. If the product accidentally gets into eyes, flush thoroughly with water. May be harmful if swallowed. In case of accidental ingestion or if skin or eye irritation occurs, call a poison control center or physician for treatment advice.

The Safety Data Sheet (SDS) provides additional occupational safety information. For product questions, to report adverse reactions, or for a copy of the Safety Data Sheet (SDS), call Elanco Product & Veterinary Support at 888-545-5973.

PRECAUTIONS:

Safe use of this product has not been evaluated in cats less than 8 weeks of age or weighing less than 2.2 lbs (1 kg), in cats used for breeding, during pregnancy or in lactating queens. The effectiveness of this product when used before bathing has not been evaluated.

Use with caution in sick or debilitated cats. Oral ingestion or exposure should be avoided. Use with caution in heartworm positive cats. The cats enrolled in the field study were heartworm antigen and antibody negative prior to entering the study. In a laboratory study, cats artificially infected with adult heartworms and treated with PROFENDER Topical Solution had fewer worms recovered than the placebo control group. (See ANIMAL SAFETY.)

ADVERSE REACTIONS:

Field study: In a controlled, double-masked field safety study, owners administered PROFENDER Topical Solution to 606 cats. Adverse reactions reported by the cat owners included licking/excessive grooming in 18 cats (3.0%), scratching treatment site in 15 cats (2.5%), salivation in 10 cats (1.7%), lethargy in 10 cats (1.7%), alopecia in 8 cats (1.3%), agitation/nervousness in 7 cats (1.2%), vomiting in 6 cats (1.0%), diarrhea in 3 cats (0.5%), eye irritation in 3 cats (0.5%), respiratory irritation in 1 cat (0.2%) and shaking/tremors in 1 cat (0.2%). All adverse reactions were self-limiting.

Laboratory effectiveness studies: One cat died 10 days after receiving PROFENDER Topical Solution. The necropsy showed chronic active cholangiohepatitis. While the use of the drug did not appear to be the direct cause of death, treatment with the drug cannot be ruled out as a contributing factor (See PRECAUTIONS). One cat treated with a vehicle placebo (formulation minus the active ingredients) showed salivation, gagging, lethargy and a swollen tongue.

Foreign Market Experience: The following adverse events were reported voluntarily during post-approval use of the product in foreign markets: application site reaction (hair loss, dermatitis, pyoderma, edema, and erythema), salivation, pruritus, lethargy, vomiting, diarrhea, dehydration, ataxia, loss of appetite, facial swelling, rear leg paresis, seizures, hyperesthesia, twitching, and death.

Post-Approval Experience: The following adverse events are based on post-approval adverse drug experience reporting. Not all adverse events are reported to FDA CVM. It is not always possible to reliably estimate the adverse event frequency or establish a causal relationship to product exposure using this data. The following adverse events are listed in decreasing order of reporting frequency in cats: Application site reaction (hair loss, dermatitis, pyoderma, edema, and erythema), hypersalivation, lethargy/depression, vomiting, ataxia, anorexia, trembling/twitching, diarrhea, mydriasis, fever, hyper-activity/nervousness. In some cases, death has been reported as an outcome of the adverse events listed. For a complete listing of the adverse reactions for Profender Topical Solution reported to the CVM see: http://www.fda.gov/ADEreports.

This listing includes Adverse Events reported to CVM for products, such as Profender, that contain the combined active ingredients emodepside and praziquantel. Listings by active ingredient may represent more than one brand name.

CONTACT INFORMATION:

For product questions, to report adverse reactions, or for a copy of the Safety Data Sheet (SDS), call Elanco Product & Veterinary Support at 888-545-5973. For additional information about reporting adverse drug experiences for animal drugs, contact FDA at 1-888-FDA-VETS or http://www.fda.gov/reportanimalae.

EFFECTIVENESS:

In a total of 13 controlled laboratory studies to establish effectiveness, 149 cats were treated with PROFENDER Topical Solution. In the field study conducted at 13 veterinary clinics/hospitals, 837 purebred or crossbred cats from single and multi-cat households were enrolled to evaluate safety and effectiveness under field conditions of use. Of those, 606 received a single treatment with PROFENDER Topical Solution. Cats ranged in age between 2 months and 17 years and weighed between 0.8 lbs (0.36 kg) and 21 lbs (9.62 kg). Data from these studies demonstrated PROFENDER Topical Solution is safe and effective for the treatment and control of hookworm infections caused by Ancylostoma tubaeforme (adults, immature adults, and fourth stage larvae), roundworm infections caused by Toxocara cati (adults and fourth stage larvae), and tapeworm infections caused by Dipylidium caninum (adults) and Taenia taeniaeformis (adults).

ANIMAL SAFETY:

In a field study, PROFENDER Topical Solution was used in cats receiving other frequently used products including: analgesics, anti-fungals, non-steroidal anti-inflammatories, anthelmintics, antimicrobials, flea and tick products, sedatives, anesthetics, cardiac medications, anxiolytics, hormonal treatments, steroids, otic and ophthalmic preparations, and vaccines.

Dose Tolerance Study in Cats: PROFENDER Topical Solution was applied topically one time to young cats at 10X the recommended label use rate. Two cats salivated. Another cat exhibited tremors and lethargy. These signs were self-limiting.

Oral Safety Studies in Cats: PROFENDER Topical Solution was administered orally at the recommended topical dose to young adult cats. The cats exhibited salivation, vomiting, tremors, abnormal gait, abnormal respiration and weight loss. These signs were self-limiting.

General Safety Study in Kittens: PROFENDER Topical Solution was topically applied at 0X (vehicle control), 1X, 3X and 5X the maximum dose to 48 healthy 8-week-old kittens every two weeks for six doses. One 5X kitten experienced salivation and tremors and another 5X kitten experienced salivation on the day of dosing. A third 5X kitten experienced tremors the day after dosing. Three cats vomited within 24 hours of dosing, one each in vehicle control, 3X and 5X groups.

Safety Study in Heartworm Positive Cats: Cats artificially infected with adult heartworms harvested from dogs were treated topically with PROFENDER Topical Solution at 0X, 1X or 5X the recommended dose once a month for three treatments. Clinical signs included salivation (one 1X and three 5X cats), labored breathing (all groups) and lethargy (one 5X cat). At the study conclusion, the 1X and 5X cats had fewer live heartworms recovered than the 0X group.

STORAGE INFORMATION:

Store at or below 77º F (25º C).

Protect from freezing.

HOW SUPPLIED:

Applications per Package

8 - 0.35 mL tubes (2 blisters of 4 tubes)

Variety Pack

20 - 0.7 mL tubes (5 blisters of 4 tubes)

8 - 1.12 mL tubes (2 blisters of 4 tubes)

20 - 0.35 mL tubes (5 blisters of 4 tubes)

40 - 0.35 mL tubes (10 blisters of 4 tubes)

20 - 0.7 mL tubes (5 blisters of 4 tubes)

40 - 0.7 mL tubes (10 blisters of 4 tubes)

20 - 1.12 mL tubes (5 blisters of 4 tubes)

40 - 1.12 mL tubes (10 blisters of 4 tubes)

Product of Germany

Approved by FDA under NADA # 141-275

Manufactured for:
Elanco US Inc.
Indianapolis, IN 46221 U.S.A
©2025 Elanco or its affiliates.

Profender, Elanco and the diagonal bar logo are trademarks of Elanco or its affiliates.

Revised: August 2025
ElancoTM

Principal Display Panel - 0.35 mL Carton Label

convenient, easy to apply

Topical Solution

profender™

(emodepside/praziquantel)

CAUTION: Federal law restricts this drug to use by or on the order of a licensed veterinarian.

Topical Solution for the treatment and control of hookworm, roundworm and tapeworm infections.

Small

For Cats and Kittens

8 weeks of age and older and weighing at least 2.2-5.5 lbs.

Contains 20 - 0.35 ml tubes

20 tubes

Each tube contains 7.5 mg of emodepside and 30 mg of praziquantel.

Approved by FDA under NADA# 141-275

Elanco™

convenient, easy to apply

Topical Solution

profender™

(emodepside/praziquantel)

CAUTION: Federal law restricts this drug to use by or on the order of a licensed veterinarian.

Topical Solution for the treatment and control of hookworm, roundworm and tapeworm infections.

Small

For Cats and Kittens

8 weeks of age and older and weighing at least 2.2-5.5 lbs.

Contains 40 - 0.35 ml tubes

40 tubes

Each tube contains 7.5 mg of emodepside and 30 mg of praziquantel.

Approved by FDA under NADA# 141-275

Elanco™

Principal Display Panel - 0.35 mL Blister Pack Label

Topical Solution

profender™

(emodepside/praziquantel)

(7.5 mg emodepside + 30 mg praziquantel)

Small

For cats and kittens 2.2 - 5.5 lbs.

0.35 mL

90209924

FL502557A

Store at or below 77°F (25°C). Protect from freezing.

See package insert for safety and administration information prior to use. Made in Germany.

© 2022 Elanco or its affiliates.

Approved by FDA under NADA #141-275

Elanco

LOT:
EXP:

Principal Display Panel - 0.35 mL Tube Label

Elanco

Topical Solution

profender™

(emodepside/praziquantel)

(7.5 mg emodepside + 30 mg praziquantel)

For cats 2.2 - 5.5 lbs.

0.35 mL

YL502557H

Lot No.

Exp.

90209927

Principal Display Panel - 0.70 mL Carton Label

convenient, easy to apply

Topical Solution

profender™

(emodepside/praziquantel)

CAUTION: Federal law restricts this drug to use by or on the order of a licensed veterinarian.

Topical Solution for the treatment and control of hookworm, roundworm and tapeworm infections.

Medium

For Cats and Kittens

8 weeks of age and older and weighing > 5.5 - 11 lbs.

Contains 20 - 0.70 ml tubes

20 tubes

Each tube contains 15 mg of emodepside and 60.1 mg of praziquantel.

Approved by FDA under NADA# 141-275

Elanco™

convenient, easy to apply

Topical Solution

profender™

(emodepside/praziquantel)

CAUTION: Federal law restricts this drug to use by or on the order of a licensed veterinarian.

Topical Solution for the treatment and control of hookworm, roundworm and tapeworm infections.

Medium

For Cats and Kittens

8 weeks of age and older and weighing > 5.5 - 11 lbs.

Contains 40 - 0.70 ml tubes

40 tubes

Each tube contains 15 mg of emodepside and 60.1 mg of praziquantel.

Approved by FDA under NADA# 141-275

Elanco™

Principal Display Panel - 0.70 mL Blister Pack Label

Topical Solution

profender™

(emodepside/praziquantel)

(15 mg emodepside + 60.1 mg praziquantel)

Medium

For cats and kittens > 5.5 - 11 lbs.

0.70 mL

90209925

FL502557B

Store at or below 77°F (25°C). Protect from freezing.

See package insert for safety and administration information prior to use. Made in Germany.

© 2022 Elanco or its affiliates.

Approved by FDA under NADA #141-275

Elanco

LOT:
EXP:

Principal Display Panel - 0.70 mL Tube Label

Elanco

Topical Solution

profender™

(emodepside/praziquantel)

(15 mg emodepside + 60.1 mg praziquantel)

For cats > 5.5 - 11 lbs.

0.70 mL

YL502557I

Lot No.

Exp.

90209928

Principal Display Panel - 1.12 mL Carton Label

convenient, easy to apply

Topical Solution

profender™

(emodepside/praziquantel)

CAUTION: Federal law restricts this drug to use by or on the order of a licensed veterinarian.

Topical Solution for the treatment and control of hookworm, roundworm and tapeworm infections.

Large

For Cats and Kittens

8 weeks of age and older and weighing > 11 – 17.6 lbs.

Contains 20 – 1.12 ml tubes

20 tubes

Each tube contains 24 mg of emodepside and 96.1 mg of praziquantel.

Approved by FDA under NADA# 141-275

Elanco™

convenient, easy to apply

Topical Solution

profender™

(emodepside/praziquantel)

CAUTION: Federal law restricts this drug to use by or on the order of a licensed veterinarian.

Topical Solution for the treatment and control of hookworm, roundworm and tapeworm infections.

Large

For Cats and Kittens

8 weeks of age and older and weighing > 11 – 17.6 lbs.

Contains 40 – 1.12 ml tubes

40 tubes

Each tube contains 24 mg of emodepside and 96.1 mg of praziquantel.

Approved by FDA under NADA# 141-275

Elanco™

Principal Display Panel - 1.12 mL Blister Pack Label

Topical Solution

profender™

(emodepside/praziquantel)

(24 mg emodepside + 96.1 mg praziquantel)

Large

For cats > 11 - 17.6 lbs.

1.12 mL

90209926

FL502257C

Store at or below 77°F (25°C). Protect from freezing.

See package insert for safety and administration information prior to use. Made in Germany.

© 2022 Elanco or its affiliates.

Approved by FDA under NADA #141-275

Elanco

LOT:
EXP:

Principal Display Panel - 1.12 mL Tube Label

Elanco

Topical Solution

profender™

(emodepside/praziquantel)

(24 mg emodepside + 96.1 mg praziquantel)

For cats > 11 - 17.6 lbs.

1.12 mL

YL502557J

90209929

Lot No.

Exp.

Principal Display Panel - Kit Label

Topical Solution

profender™

(emodepside/praziquantel)

ElancoTM

8
tubes

Small

For Cats and Kittens

8 weeks of age and older and weighing > 2.2-5.5 lbs

Contains 8 - 0.35 ml tubes

Each tube contains 7.5 mg of emodepside and 30 mg of praziquantel.

20
tubes

Medium

For Cats and Kittens

8 weeks of age and older and weighing > 5.5-11 lbs

Contains 20 - 0.70 ml tubes

Each tube contains 15 mg of emodepside and 60.1 mg of praziquantel.

8
tubes

Large

For Cats and Kittens

8 weeks of age and older and weighing > 11-17.6 lbs

Contains 8 - 1.12 ml tubes

Each tube contains 24 mg of emodepside and 96.1 mg of praziquantel.

Lot No.:

Exp.:

Do not dispense dose applicator without complete safety and administration information.

Elanco™

Topical Solution

profender™

(emodepside/praziquantel)

convenient, easy to apply

Do not dispense dose applicator without complete safety and administration information.

Indicated for the treatment and control of hookworm infections caused by Ancylostoma tubaeforme (adults, immature adult and fourth stage larvae), roundworm infections caused by Toxocara cati (adults and fourth stage larvae), and tapeworm infections caused by Dipylidium caninum (adults) and Taenia taeniaeformis (adults) in cats.

HUMAN WARNINGS: Not for human use. Keep out of reach of children.
To prevent accidental ingestion of the product, children should not come into contact with the application site for twenty-four (24) hours while the product is being absorbed.

See package insert for complete product information.

CAUTION: Federal law restricts this drug to use by or on the order of a licensed veterinarian.
Topical Solution for the treatment and control of hookworm, roundworm and tapeworm infections.

8
tubes

Small

For Cats and Kittens

8 weeks of age and older and weighing > 2.2-5.5 lbs

Contains 8 - 0.35 ml tubes

Each tube contains 7.5 mg of emodepside and 30 mg of praziquantel.

20
tubes

Medium

For Cats and Kittens

8 weeks of age and older and weighing > 5.5-11 lbs

Contains 20 - 0.70 ml tubes

Each tube contains 15 mg of emodepside and 60.1 mg of praziquantel.

8
tubes

Large

For Cats and Kittens

8 weeks of age and older and weighing > 11-17.6 lbs

Contains 8 - 1.12 ml tubes

Each tube contains 24 mg of emodepside and 96.1 mg of praziquantel.

See package insert for complete product information.